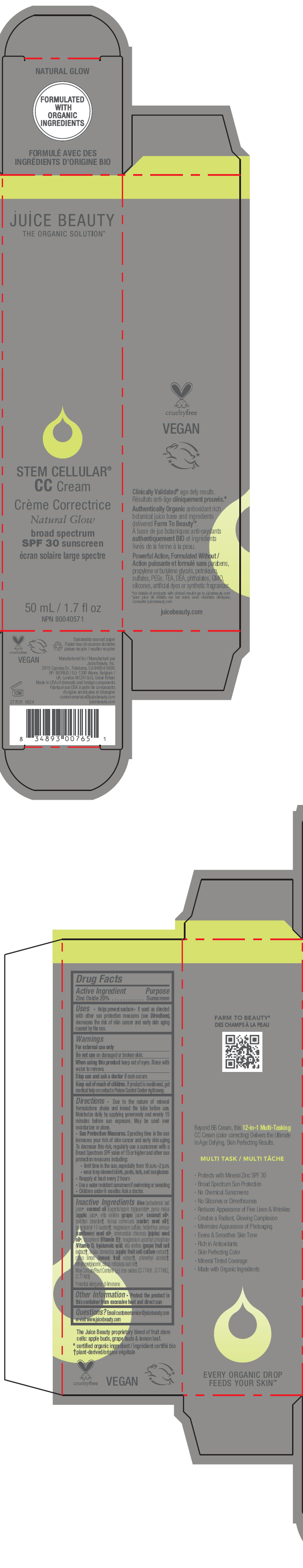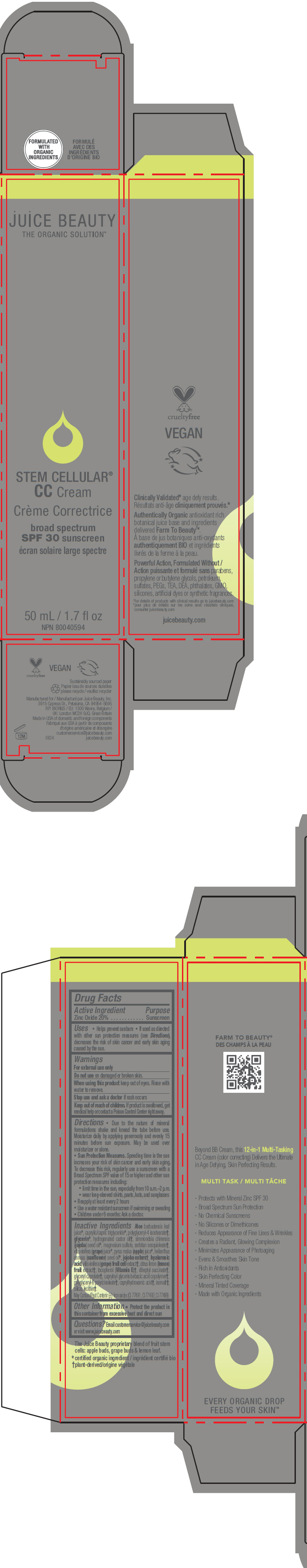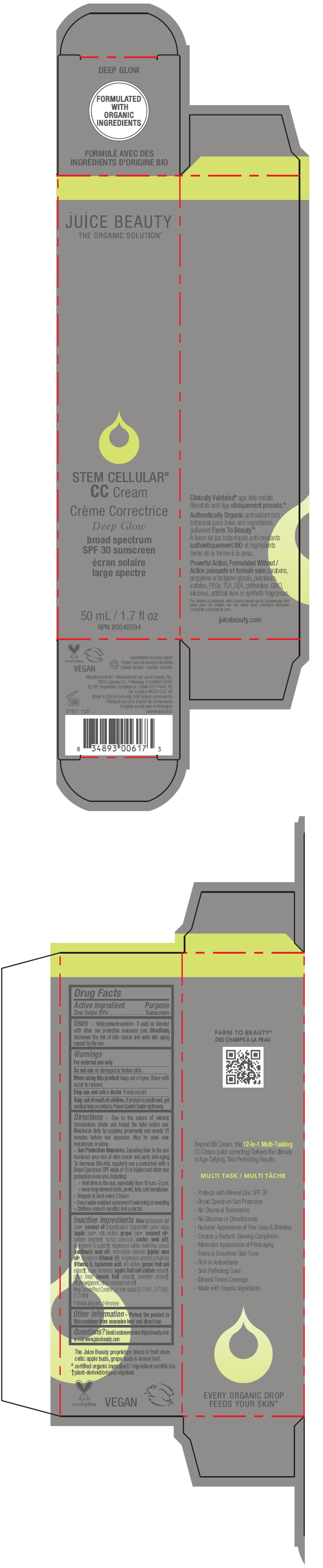 DRUG LABEL: Stem Cellular CC Cream natural glow
NDC: 55165-1001 | Form: LOTION
Manufacturer: Juice Beauty
Category: otc | Type: HUMAN OTC DRUG LABEL
Date: 20241223

ACTIVE INGREDIENTS: Zinc Oxide 20 g/100 mL
INACTIVE INGREDIENTS: ALOE VERA LEAF; MEDIUM-CHAIN TRIGLYCERIDES; SORBITAN MONOSTEARATE; COCONUT OIL; WINE GRAPE JUICE; APPLE JUICE; CASTOR ACID; glycerin; POLYGLYCERYL-10 LAURATE; MAGNESIUM SULFATE, UNSPECIFIED FORM; SUNFLOWER OIL; JOJOBA OIL; TOCOPHEROL; MAGNESIUM ASCORBYL PHOSPHATE; hyaluronic acid; WINE GRAPE; APPLE; LEMON; PHENYLETHYL ALCOHOL; ethylhexylglycerin

Stem Cellular™ CC Cream

Drug Facts

Active Ingredient

Zinc Oxide 20%

Purpose

Sunscreen

Uses

- Helps prevent sunburn
- If used as directed with other sun protection measures (see Directions), decreases the risk of skin cancer and early skin aging caused by the sun.

Warnings

For external use only

Do not use on damaged or broken skin.

When using this product keep out of eyes. Rinse with water to remove.

Stop use and ask a doctor if rash occurs

Keep out of reach of children. If product is swallowed, get medical help or contact a Poison Control Center right away.

Directions

- Due to the nature of mineral formulations shake and knead the tube before use. Moisturize daily by applying generously and evenly 15 minutes before sun exposure. May be used over moisturizer or alone.
- Sun Protection Measures. Spending time in the sun increases your risk of skin cancer and early skin aging. To decrease this risk, regularly use a sunscreen with a Broad Spectrum SPF value of 15 or higher and other sun protection measures including:
  - limit time in the sun, especially from 10 a.m.–2 p.m.
  - wear long-sleeved shirts, pants, hats, and sunglasses
- Reapply at least every 2 hours
- Use a water resistant sunscreen if swimming or sweating
- Children under 6 months: Ask a doctor.

Inactive Ingredients

Shade | Inactive ingredient
Natural Glow | Aloe barbadensis leaf juice [certified organic ingredient / ingrédient certifié bio] , caprylic/capric triglyceride, sorbitan stearate [plant-derived/origine végétale] , cocos nucifera (coconut) oil, vitis vinifera (grape) juice, pyrus malus (apple) juice, ricinus communis (castor) seed oil, glycerin, polyglyceryl-10 laurate, magnesium sulfate, helianthus annuus (sunflower) seed oil, simmondsia chinensis (jojoba) seed oil, tocopherol (Vitamin E), magnesium ascorbyl phosphate (Vitamin C), hyaluronic acid, vitis vinifera (grape) fruit cell extract, malus domestica fruit cell culture extract, citrus limon (lemon) fruit extract, phenethyl alcohol, ethylhexylglycerin. May Contain/Peut Contenir (±): iron oxides (CI 77491, CI 77492, CI 77499)
Rosy Glow Beach Glow Desert Glow Warm Glow Island Glow Sun-Kissed Glow | Aloe barbadensis leaf juice, caprylic/capric triglyceride, polyglyceryl-4 isostearate, glycerin, hydrogenated castor oil, simmondsia chinensis (jojoba) seed oil, magnesium sulfate, sorbitan sesquioleate, vitis vinifera (grape) juice, pyrus malus (apple) juice, helianthus annuus (sunflower) seed oil, jojoba esters, hyaluronic acid, vitis vinifera (grape) fruit cell extract, citrus limon (lemon) fruit extract, tocopherol (Vitamin E), diheptyl succinate, glyceryl caprylate, capryloyl glycerin/sebacic acid copolymer, polyglyceryl-6 polyricinoleate, caprylhydroxamic acid, isomalt, silica, lecithin. May Contain (±): iron oxides (CI 77491, CI 77492, CI 77499)
Deep Glow | Aloe barbadensis leaf juice, coconut oil (caprylic/capric triglyceride), pyrus malus (apple) juice, vitis vinifera (grape) juice, coconut oil, sorbitan stearate, ricinus communis (castor) seed oil, polyglyceryl-10 laurate, magnesium sulfate, helianthus annuus (sunflower) seed oil, simmondsia chinensis (jojoba) seed oil, tocopherol (Vitamin E), magnesium ascorbyl phosphate (Vitamin C), hyaluronic acid, vitis vinifera (grape) fruit cell extract, malus domestica (apple) fruit cell culture extract, citrus limon (lemon) fruit extract, phenethyl alcohol, ethylhexylglycerin, citrus reticulata leaf oil. May Contain (±): iron oxides (CI 77491, CI 77492, CI 77499) Potential allergens: d-limonene

Other Information

- Protect the product in this container from excessive heat and direct sun

Questions?

www.juicebeauty.com

PRINCIPAL DISPLAY PANEL - 50 mL Tube Carton - Natural

juice BEAUTY
THE ORGANIC SOLUTION™

STEM CELLULAR®
CC Cream

Natural Glow

broad spectrum
SPF 30 sunscreen

50 mL / 1.7 fl oz
NPN 80040571

PRINCIPAL DISPLAY PANEL - 50 mL Tube Carton - Rosy

juice BEAUTY
THE ORGANIC SOLUTION™

STEM CELLULAR®
CC Cream

broad spectrum
SPF 30 sunscreen

50 mL / 1.7 fl oz
NPN 80040594

PRINCIPAL DISPLAY PANEL - 50 mL Tube Carton - Beach

juice BEAUTY
THE ORGANIC SOLUTION™

STEM CELLULAR®
CC Cream

broad spectrum
SPF 30 sunscreen

50 mL / 1.7 fl oz
NPN 80040594

PRINCIPAL DISPLAY PANEL - 50 mL Tube Carton - Desert

juice BEAUTY
THE ORGANIC SOLUTION™

STEM CELLULAR®
CC Cream

broad spectrum
SPF 30 sunscreen

50 mL / 1.7 fl oz
NPN 80040594

PRINCIPAL DISPLAY PANEL - 50 mL Tube Carton - Warm

juice BEAUTY
THE ORGANIC SOLUTION™

STEM CELLULAR®
CC Cream

broad spectrum
SPF 30 sunscreen

50 mL / 1.7 fl oz
NPN 80040594

PRINCIPAL DISPLAY PANEL - 50 mL Tube Carton - Sun-Kissed

juice BEAUTY
THE ORGANIC SOLUTION™

STEM CELLULAR®
CC Cream

broad spectrum
SPF 30 sunscreen

50 mL / 1.7 fl oz
NPN 80040594

PRINCIPAL DISPLAY PANEL - 50 mL Tube Carton - Deep

juice BEAUTY
THE ORGANIC SOLUTION™

STEM CELLULAR®
CC Cream

Deep Glow

broad spectrum
SPF 30 sunscreen

50 mL / 1.7 fl oz
NPN 80040594

PRINCIPAL DISPLAY PANEL - 50 mL Tube Carton - Island Glow

juice BEAUTY
THE ORGANIC SOLUTION™

STEM CELLULAR®
CC Cream

broad spectrum
SPF 30 sunscreen

50 mL / 1.7 fl oz
NPN 80040594